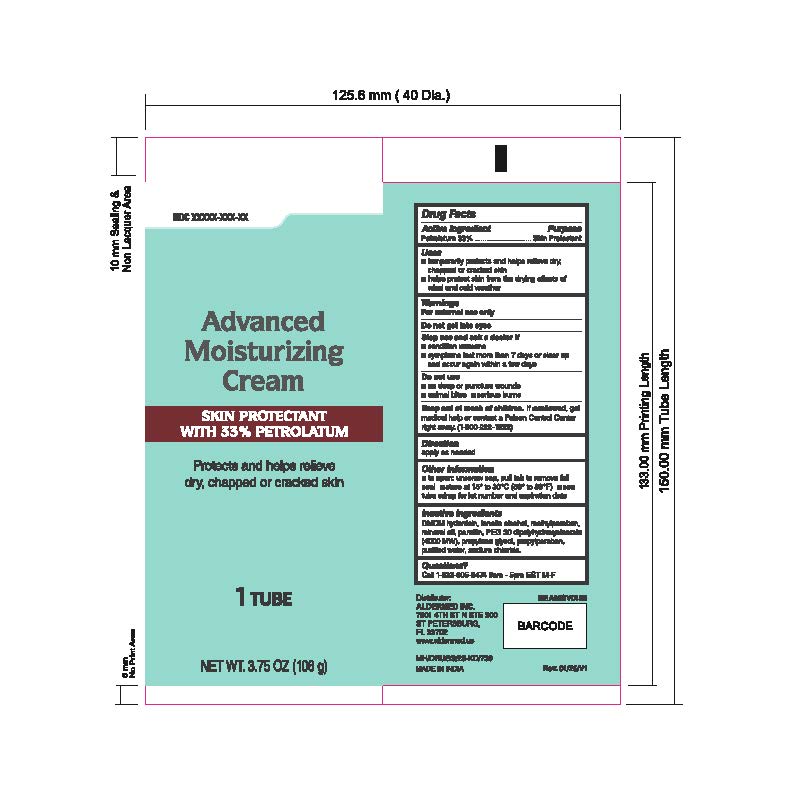 DRUG LABEL: Skin Protectant with 33% Petrolatum
NDC: 87236-011 | Form: CREAM
Manufacturer: Aldermed Inc.
Category: otc | Type: HUMAN OTC DRUG LABEL
Date: 20260212

ACTIVE INGREDIENTS: PETROLATUM 33 g/100 g
INACTIVE INGREDIENTS: PROPYLPARABEN; SODIUM CHLORIDE; WATER; PARAFFIN; PEG-30 DIPOLYHYDROXYSTEARATE; LANOLIN ALCOHOLS; DMDM HYDANTOIN; MINERAL OIL; METHYLPARABEN; PROPYLENE GLYCOL

Skin Protectant with 33% Petrolatum

Active ingredient

Petrolatum 33%

Purpose

Skin Protectant

Use(s)

• Temporarily protects and helps relieve dry, chapped, or cracked skin

• Helps protect skin from the drying effects of wind and cold weather

Warnings

For External Use Only

Do not get into eyes

Stop use and ask a doctor if

- Conditions worsens
- Symptoms last more than 7 days or clear up and occur again within a few days

Do not use

• On deep puncture wounds • Animal bites • Serious burns.

Keep out of reach of children

If swallowed, get medical help or contact a Poison Control Center (1-800-222-1222) right away.

Directions

Apply as needed

Other information

■ to open: unscrew cap, pull tab to remove foil seal

■ store at 15° to 30°C (59° to 86°F)

■ see tube crimp for lot number and expiration date

Inactive Ingredients

DMDM Hydantoin, Lanolin Alcohol, Methyl Paraben, Mineral Oil, Paraffin, PEG 30 Dipolyhydroxystearate, Propylene Glycol, Propylparaben, Purified Water, Sodium Chloride

Questions?

Call 1-833-605-84-74 9am-5 pm EST M-F